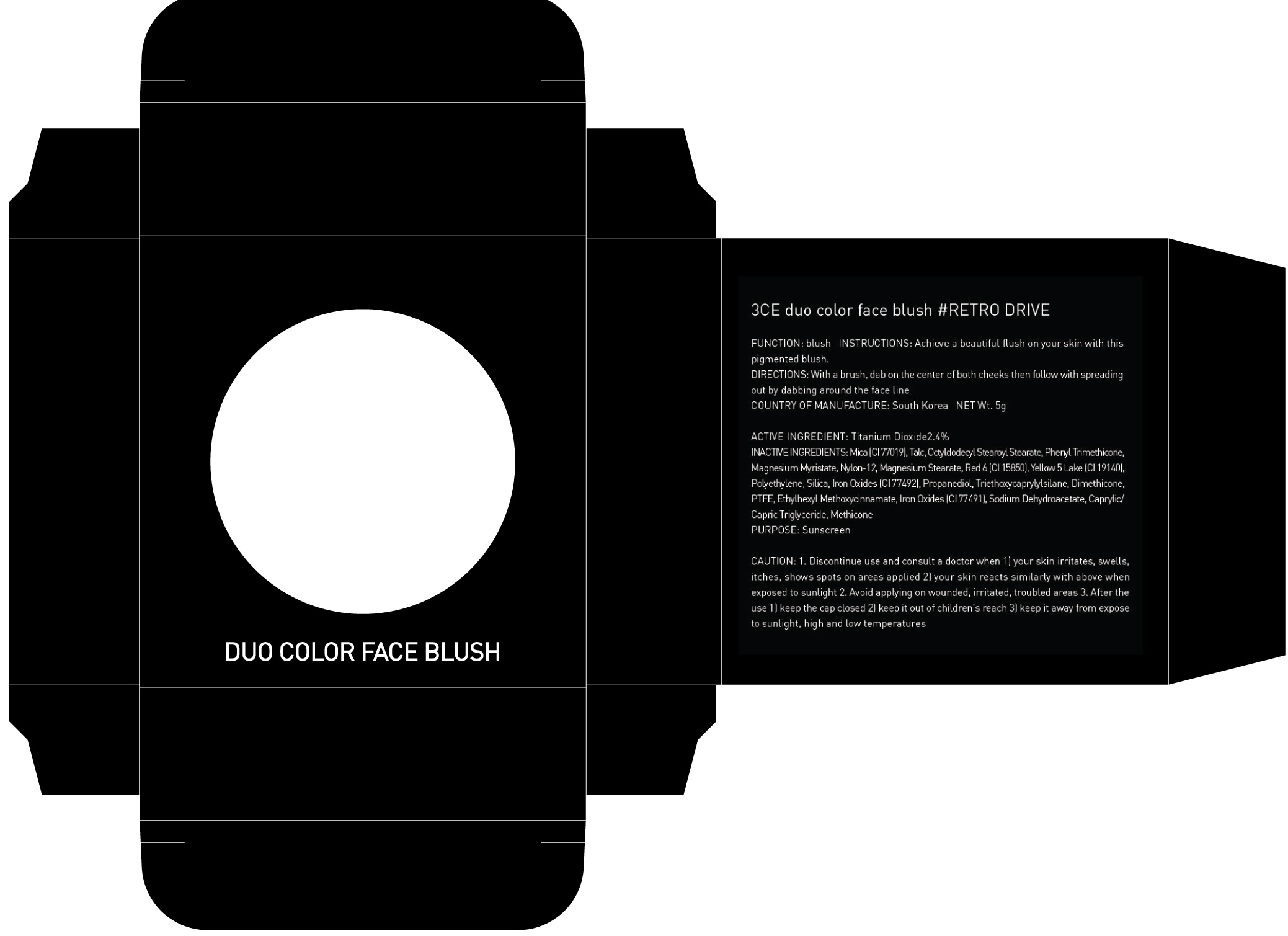 DRUG LABEL: 3CE DUO COLOR FACE BLUSH RETRO DRIVE
NDC: 60764-061 | Form: POWDER
Manufacturer: Nanda Co., Ltd
Category: otc | Type: HUMAN OTC DRUG LABEL
Date: 20161004

ACTIVE INGREDIENTS: Titanium Dioxide 0.12 g/5 g
INACTIVE INGREDIENTS: Mica; Talc

ACTIVE INGREDIENT

Active Ingredient: Titanium Dioxide 2.4%

INACTIVE INGREDIENT

Inactive Ingredients: Mica (CI 77019), Talc, Octyldodecyl Stearoyl Stearate, Phenyl Trimethicone, Magnesium Myristate, Nylon-12, Magnesium Stearate, Red 6 (CI 15850), Yellow 5 Lake (CI 19140), Polyethylene, Silica, Iron Oxides (CI 77492), Propanediol, Triethoxycaprylylsilane, Dimethicone, PTFE, Ethylhexyl Methoxycinnamate, Iron Oxides (CI 77491), Sodium Dehydroacetate, Caprylic/Capric Triglyceride, Methicone

PURPOSE

Purpose: Sunscreen

CAUTION

CAUTION: 1. Discontinue use and consult a doctor when - your skin irritates, swells, itches, shows spots on areas applied - your skin reacts similarly with above when exposed to sunlight 2. Avoid applying on wounded, irritated, troubled areas 3. After the use - keep the cap closed - keep it out of children's reach - keep it away from expose to sunlight, high and low temperatures

DESCRIPTION

INSTRUCTIONS: Achieve a beautiful flush on your skin with this pigmented blush.

Directions: With a brush, dab on the center of both cheeks then follow with spreading out by dabbing around the face line